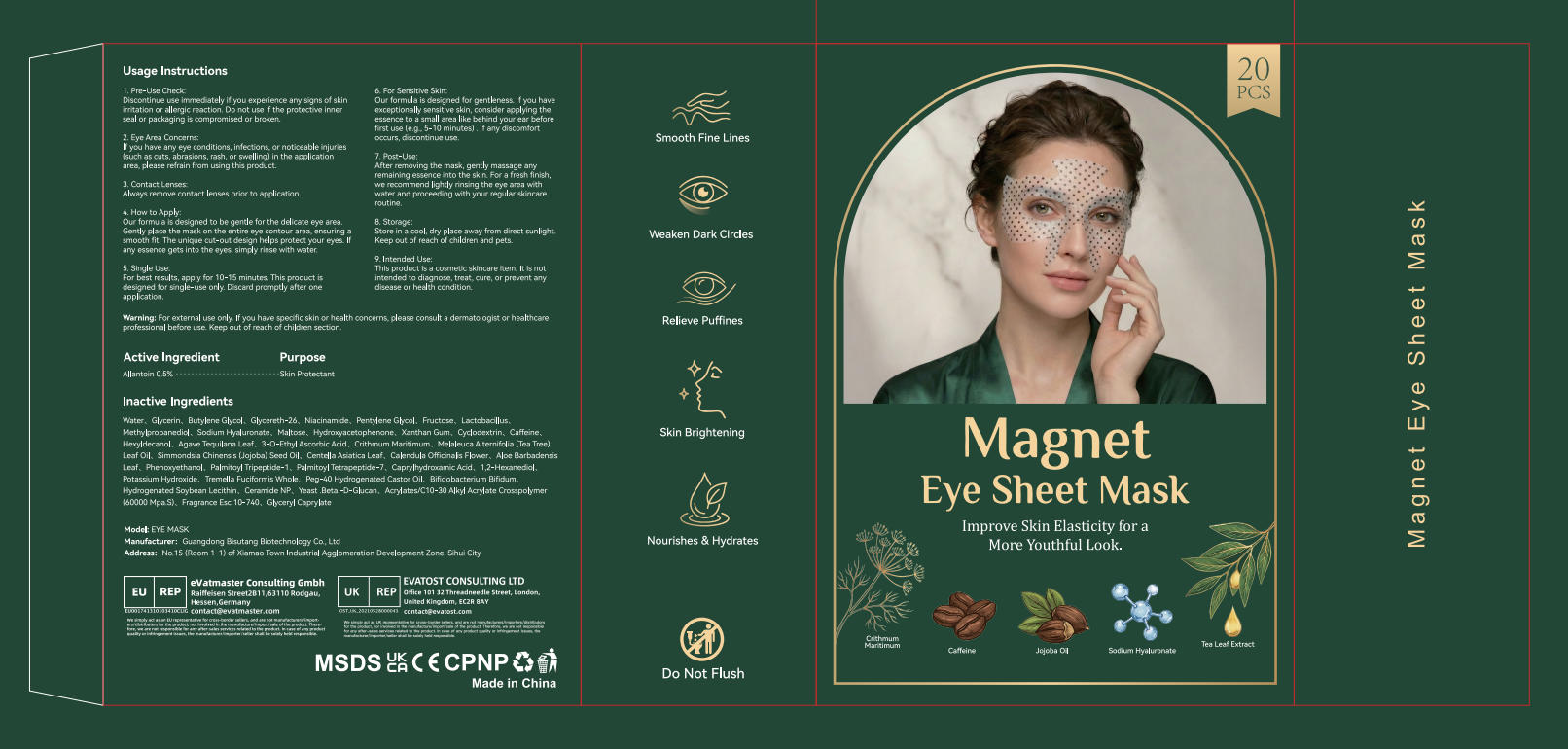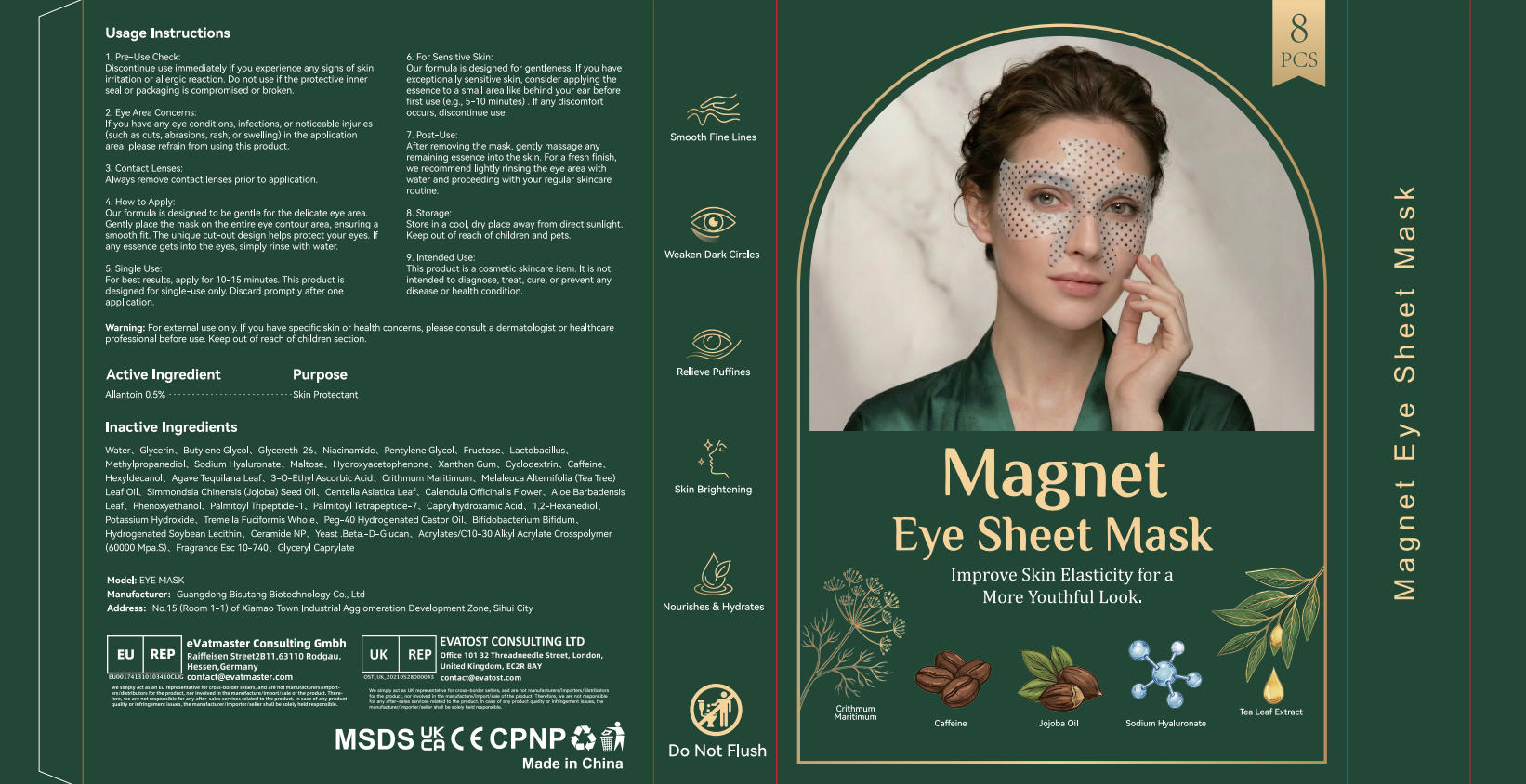 DRUG LABEL: Magnet Eye Sheet Mask
NDC: 84753-039 | Form: PATCH
Manufacturer: Guangdong Bisutang Biotechnology Co., LTD
Category: otc | Type: HUMAN OTC DRUG LABEL
Date: 20260224

ACTIVE INGREDIENTS: ALLANTOIN 0.5 mg/100 g
INACTIVE INGREDIENTS: GLYCERIN; FRUCTOSE; LACTOBACILLUS; AGAVE TEQUILANA LEAF; PEG-40 HYDROGENATED CASTOR OIL; PALMITOYL TRIPEPTIDE-1; CAPRYLHYDROXAMIC ACID; TREMELLA FUCIFORMIS WHOLE; CYCLODEXTRIN; NIACINAMIDE; HEXYLDECANOL; ACRYLATES/C10-30 ALKYL ACRYLATE CROSSPOLYMER (60000 MPA.S); PHENOXYETHANOL; PENTYLENE GLYCOL; CAFFEINE; FRAGRANCE ESC 10-740; POTASSIUM HYDROXIDE; METHYLPROPANEDIOL; 1,2-HEXANEDIOL; CRITHMUM MARITIMUM; MELALEUCA ALTERNIFOLIA (TEA TREE) LEAF OIL; SIMMONDSIA CHINENSIS (JOJOBA) SEED OIL; GLYCERETH-26; MALTOSE; 3-O-ETHYL ASCORBIC ACID; CALENDULA OFFICINALIS FLOWER; SODIUM HYALURONATE; YEAST .BETA.-D-GLUCAN; ALOE BARBADENSIS LEAF; CERAMIDE NP; BIFIDOBACTERIUM BIFIDUM; PALMITOYL TETRAPEPTIDE-7; WATER; BUTYLENE GLYCOL; HYDROXYACETOPHENONE; HYDROGENATED SOYBEAN LECITHIN; GLYCERYL CAPRYLATE; CENTELLA ASIATICA LEAF; XANTHAN GUM

INACTIVE INGREDIENT

WATER
GLYCERIN
BUTYLENE GLYCOL
GLYCERETH-26
NIACINAMIDE
PENTYLENE GLYCOL
FRUCTOSE
LACTOBACILLUS
METHYLPROPANEDIOL
SODIUM HYALURONATE
MALTOSE
HYDROXYACETOPHENONE
XANTHAN GUM
CYCLODEXTRIN
CAFFEINE
HEXYLDECANOL
AGAVE TEQUILANA LEAF
3-O-ETHYL ASCORBIC ACID
ACRYLATES/C10-30 ALKYL ACRYLATE CROSSPOLYMER (60000 MPA.S)
CAPRYLHYDROXAMIC ACID
1,2-HEXANEDIOL
POTASSIUM HYDROXIDE
TREMELLA FUCIFORMIS WHOLE
PEG-40 HYDROGENATED CASTOR OIL
BIFIDOBACTERIUM BIFIDUM
HYDROGENATED SOYBEAN LECITHIN
CERAMIDE NP
YEAST .BETA.-D-GLUCAN
GLYCERYL CAPRYLATE
FRAGRANCE
CRITHMUM MARITIMUM
MELALEUCA ALTERNIFOLIA (TEA TREE) LEAF OIL
SIMMONDSIA CHINENSIS (JOJOBA) SEED OIL
CENTELLA ASIATICA LEAF
CALENDULA OFFICINALIS FLOWER
ALOE BARBADENSIS LEAF
PHENOXYETHANOL
PALMITOYL TRIPEPTIDE-1
PALMITOYL TETRAPEPTIDE-7

INDICATIONS AND USAGE

How to Apply:Our formula is designed to be gentle for the delicate eye area.Gently place the mask on the entire eye contour area, ensuring asmooth fit. The unique cut-out design helps protect your eyes. Ifany essence gets into the eyes, simply rinse with water.

After removing the mask, gently massage anyremaining essence into the skin. For a fresh finish,we recommend lightly rinsing the eye area withwater and proceeding with your regular skincareroutine.

DOSAGE AND ADMINISTRATION

For best results, apply for 10-15 minutes. This product isdesigned for single-use only. Discard promptly after oneapplication.

ACTIVE INGREDIENT

ALLANTOIN------0.5%

PURPOSE

Smooth Fine Lines
Weaken Dark Circles
Relieve Puffines
Skin Brightening

Firm the skin
Enhance skin elasticity Firm the skin

KEEP OUT OF REACH OF CHILDREN.

WARNINGS

Warning: For external use only. If you have specific skin or health concerns, please consult a dermatologist or healthcare
professional before use. Keep out of reach of children section.